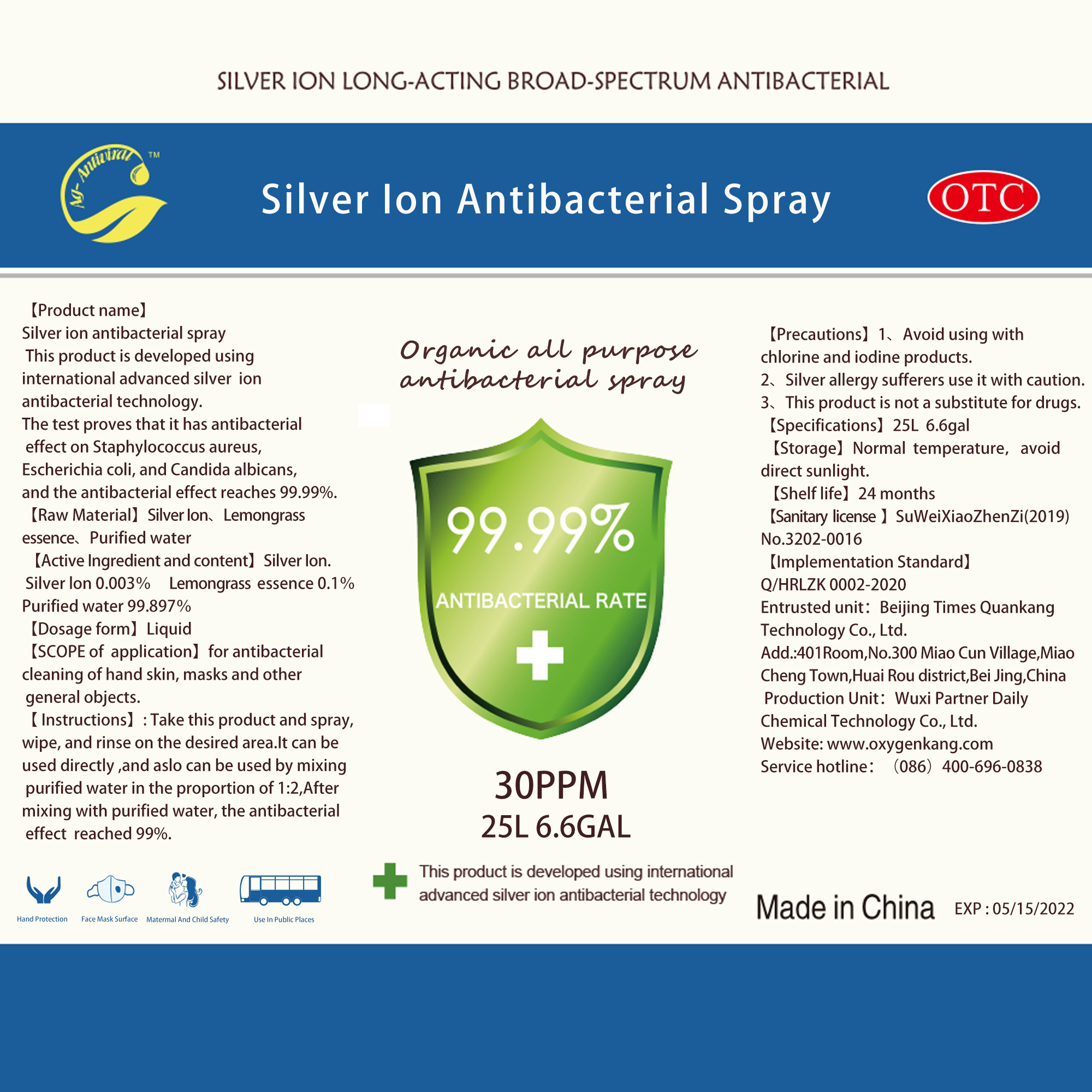 DRUG LABEL: Silver ion antibacterial
NDC: 52598-002 | Form: LIQUID
Manufacturer: Beijing Times Quankang Technology Co., Ltd.
Category: otc | Type: HUMAN OTC DRUG LABEL
Date: 20200519

ACTIVE INGREDIENTS: SILVER CATION 750 mg/25 L
INACTIVE INGREDIENTS: WATER; METHYL BENZOATE

DOSAGE AND ADMINISTRATION

Normal temperature,avoid direct sunlight.

INACTIVE INGREDIENT

Lemon essence

Purified water

INDICATIONS AND USAGE

Take this produot and spay, wipe, and rinse on the desired area.

ACTIVE INGREDIENT

Silver lon

keep out of reach of children

PURPOSE

Disinfection
Sterilization

WARNINGS

1、Avoid using with chlorine and iodine products.
2、Silver alergy sufferers use it with caution.
3、This product is not a substitute fr drugs.